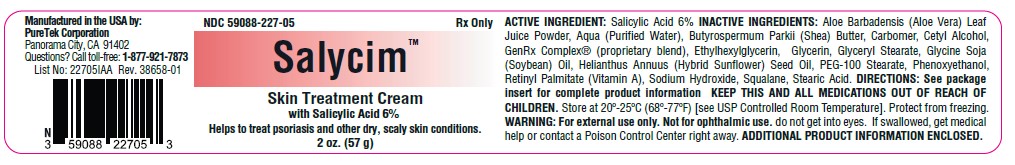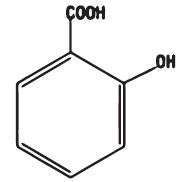 DRUG LABEL: SALYCIM
NDC: 59088-227 | Form: CREAM
Manufacturer: PURETEK CORPORATION
Category: prescription | Type: HUMAN PRESCRIPTION DRUG LABEL
Date: 20240506

ACTIVE INGREDIENTS: SALICYLIC ACID 60 mg/1 g
INACTIVE INGREDIENTS: PHENOXYETHANOL; ALOE VERA LEAF; WATER; SHEA BUTTER; CARBOMER HOMOPOLYMER, UNSPECIFIED TYPE; CETYL ALCOHOL; ETHYLHEXYLGLYCERIN; GLYCERIN; GLYCERYL MONOSTEARATE; SOYBEAN OIL; SUNFLOWER OIL; PEG-100 STEARATE; VITAMIN A PALMITATE; SODIUM HYDROXIDE; SQUALANE; STEARIC ACID

Salycim Cream
Rx Only

FOR DERMATOLOGICAL USE ONLY. NOT FOR OPHTHALMIC, ORAL OR INTRAVAGINAL USE.

INGREDIENTS

Salycim™ Cream contains 6% salicylic acid USP in a vehicle consisting of Aloe Barbadensis (Aloe Vera) Leaf Juice Powder, Aqua (Purified Water), Butyrospermum Parkii (Shea) Butter, Carbomer, Cetyl Alcohol, GenRx Complex® (proprietary blend), Ethylhexylglycerin, Glycerin, Glyceryl Stearate, Glycine Soja (Soybean) Oil, Helianthus Annuus (Hybrid Sunflower) Seed Oil, PEG-100 Stearate, Phenoxyethanol, Retinyl Palmitate (Vitamin A), Sodium Hydroxide, Squalane, Stearic Acid.

DESCRIPTION

Salicylic acid is the 2-hydroxy derivative of benzoic acid having the following structure:

CLINICAL PHARMACOLOGY

Salicylic acid has been shown to produce desquamation of the horny layer of skin while not effecting qualitative or quantitative changes in the structure of the viable epidermis. The mechanism of action has been attributed to a dissolution of intercellular cement substance. In a study of the percutaneous absorption of salicylic acid in a 6% salicylic acid gel in four patients with extensive active psoriasis, Taylor and Halprin showed that the peak serum salicylate levels never exceeded 5 mg/100 ml even though more than 60% of the applied salicylic acid was absorbed. Systemic toxic reactions are usually associated with much higher serum levels (30 to 40 mg/100 ml). Peak serum levels occurred within five hours of the topical application under occlusion. The sites were occluded for 10 hours over the entire body surface below the neck. Since salicylates are distributed in the extracellular space, patients with a contracted extracellular space due to dehydration or diuretics have higher salicylate levels than those with a normal extracellular space. (See PRECAUTIONS.)

The major metabolites identified in the urine after topical administration are salicyluric acid (52%), salicylate glucuronides (42%) and free salicylic acid (6%). The urinary metabolites after percutaneous absorption differ from those after oral salicylate administration; those derived from percutaneous absorption contain more salicylate glucuronides and less salicyluric and salicylic acid. Almost 95% of a single dose of salicylate is excreted within 24 hours of its entrance into the extracellular space. Fifty to eighty percent of salicylate is protein bound to albumin. Salicylates compete with the binding of several drugs and can modify the action of these drugs. By similar competitive mechanisms other drugs can influence the serum levels of salicylate. (See PRECAUTIONS.)

INDICATIONS AND USAGE

For Dermatologic Use: Salycim™ Cream is a topical aid in the removal of excessive keratin in hyperkeratotic skin disorders including verrucae, and the various ichthyoses (vulgaris, sex-linked and lamellar), keratosis palmaris and plantaris keratosis pilaris, pityriasis rubra pilaris, and psoriasis (including body, scalp, palms and soles).

For Podiatric Use: Salycim™ Cream is a topical aid in the removal of excessive keratin on dorsal and plantar hyperkeratotic lesions. Topical preparations of 6% salicylic acid have been reported to be useful adjunctive therapy for verrucae plantares.

CONTRAINDICATIONS

Salycim™ Cream should not be used in any patient known to be sensitive to salicylic acid or any other listed ingredients.

Salycim™ Cream should not be used in children under 2 years of age.

WARNINGS

Prolonged use over large areas, especially in children and those patients with significant renal or hepatic impairment, could result in salicylism. Concomitant use of other drugs which may contribute to elevated serum salicylate levels should be avoided where the potential for toxicity is present. In children under 12 years of age and those patients with renal or hepatic impairment, the area to be treated should be limited and the patient monitored closely for signs of salicylate toxicity: nausea, vomiting, dizziness, loss of hearing, tinnitus, lethargy, hyperpnea, diarrhea, and psychic disturbances. In the event of salicylic acid toxicity, the use of Salycim™ Cream should be discontinued. Fluids should be administered topromote urinary excretion. Treatment with sodium bicarbonate (oral or intravenous) should be instituted as appropriate.

Patients should be cautioned against the use of oral aspirin and other salicylate containing medications, such as sports injury creams, to avoid additional excessive exposure to salicylic acid.

Where needed, aspirin should be replaced by an alternative non-steroidal anti-inflammatory agent that is not salicylate based. Patients should be advised not to apply occlusive dressings, clothing or other occlusive topical products such as petrolatum-based ointments to prevent excessive systemic exposure to salicylic acid. Excessive application of the product other than what is needed to cover the affected area will not result in a more rapid therapeutic benefit.

Due to potential risk of developing Reye's syndrome, salicylate products should not be used in children and teenagers with varicella or influenza, unless directed by physician.

PRECAUTIONS

FOR EXTERNAL USE ONLY. Avoid contact with eyes and other mucous membranes.

DRUG INTERACTIONS

The following interactions are from a published review and include reports concerning both oral and topical salicylate administration. The relationship of these interactions to the use of Salycim™ Cream is not known.

I. Due to the competition of salicylate with other drugs for binding to serum albumin the following drug interactions may occur:
DRUG | DESCRIPTION OF INTERACTION
Sulfonylureas | Hypoglycemia potentiated.
Methotrexate | Decreases tubular reabsorption; clinical toxicity from methotrexate can result.
Oral Anticoagulants | Increased bleeding.
II. Drugs changing salicylate levels by altering renal tubular reabsorption:
DRUG | DESCRIPTION OF INTERACTION
Corticosteroids | Decreases plasma salicylate level; tapering doses of steroids may promote salicylism.
Acidifying Agents | Increases plasma salicylate levels.
Alkanizing Agents | Decreased plasma salicylate levels.
III. Drugs with complicated interactions with salicylates:
DRUG | DESCRIPTION OF INTERACTION
Heparin | Salicylate decreases platelet adhesiveness and interferes with hemostasis in heparin-treated patients.
Pyrazinamide | Inhibits pyrazinamide-induced hyperuricemia.
Uricosuric Agents | Effect of probenemide, sulfinpyrazone and phenylbutazone inhibited.
The following alterations of laboratory tests have been reported during salicylate therapy:
LABORATORY TESTS | EFFECT OF SALICYLATES
Thyroid Function | Decreased PBI; increased t3 uptake.
Urinary Sugar | False negative with glucose oxidase; false positive with Clinitest with high-dose salicylate therapy (2-5g q.d.).
5-Hydroxyindole acetic acid | False negative with fluorometric test.
Acetone ketone bodies | False positive FeCI3 in Gerhardt reaction; red color persists with boiling.
17-OH corticosteroids | False reduced values with >4.8g q.d. salicylate.
Vanilmandelic acid | False reduced values.
Uric Acid | May increase or decrease depending on dose.
Prothrombin | Decreased levels; slightly increased prothrombin time.

PREGNANCY

Pregnancy: Category C. Salicylic acid has been shown to be teratogenic in rats and monkeys. It is difficult to extrapolate from oral doses of acetylsalicylic acid used in these studies to topical administration as the oral dose to monkeys may represent six times the maximal daily human dose of salicylic acid when applied topically over a large body surface. There are no adequate and well-controlled studies in pregnant women. Salycim™ Cream should be used during pregnancy only if the potential benefit justifies the potential risk to the fetus.

NURSING MOTHERS

Nursing Mothers: Because of the potential for serious adverse reactions in nursing infants from the mother's use of Salycim™ Cream, a decision should be made whether to discontinue nursing or to discontinue the drug, taking into account the importance of the drug to the mother. If used by nursing mothers, it should not be used on the chest area to avoid accidental contamination of the child.

CARCINOGENESIS AND MUTAGENESIS AND IMPAIRMENT OF FERTILITY

Carcinogenesis, Mutagenesis, Impairment of Fertility: No data are available concerning potential carcinogenic or reproductive effects of Salycim™ Cream. It has been shown to lack mutagenic potential in the Ames test.

ADVERSE REACTIONS

Excessive erythema and scaling conceivably could result from use on open skin lesions. Call your physician for medical advice about side effects.

OVERDOSAGE See Warnings.

DOSAGE AND ADMINISTRATION

The preferable method of use is to apply Salycim™ Cream thoroughly to the affected area and to cover the treated area at night after washing and before retiring. Preferably, the skin should be hydrated for a least five minutes prior to application. The medication is washed off in the morning and if excessive drying and/or irritation is observed, a bland cream or lotion may be applied. Once clearing is apparent, the occasional use of Salycim™ Cream will usually maintain the remission. In those areas where occlusion is difficult or impossible, application may be made more frequently; hydration by wet packs or baths prior to application apparently enhances the effect. (See WARNINGS.) Unless hands are being treated, hands should be rinsed thoroughly after application. Excessive repeated application of Salycim™ Cream will not necessarily increase its therapeutic benefit, but could result in increased local intolerance and systemic adverse effects such as salicylism.

HOW SUPPLIED:

Salycim™ Cream is available in 2 oz (57 g) Jar, NDC 59088-227-05

STORAGE AND HANDLING

Store at 20° to 25°C (68° to 77°F) [see USP Controlled Room Temperature].
Protect from freezing and excessive heat. Keep container tightly closed.

KEEP THIS AND ALL MEDICATIONS OUT OF THE REACH OF CHILDREN.
Manufactured in the USA by:
PureTek Corporation
Panorama City, CA 91402
For questions or information
call toll-free: 877-921-7873